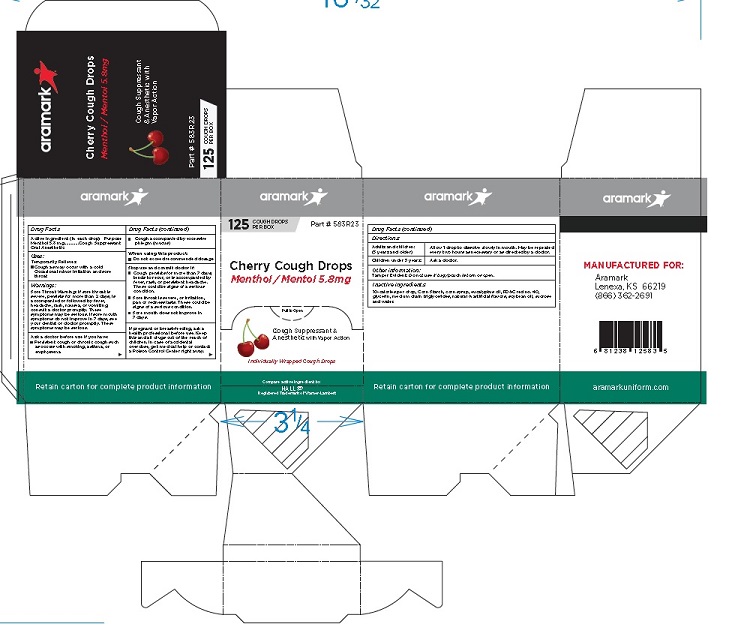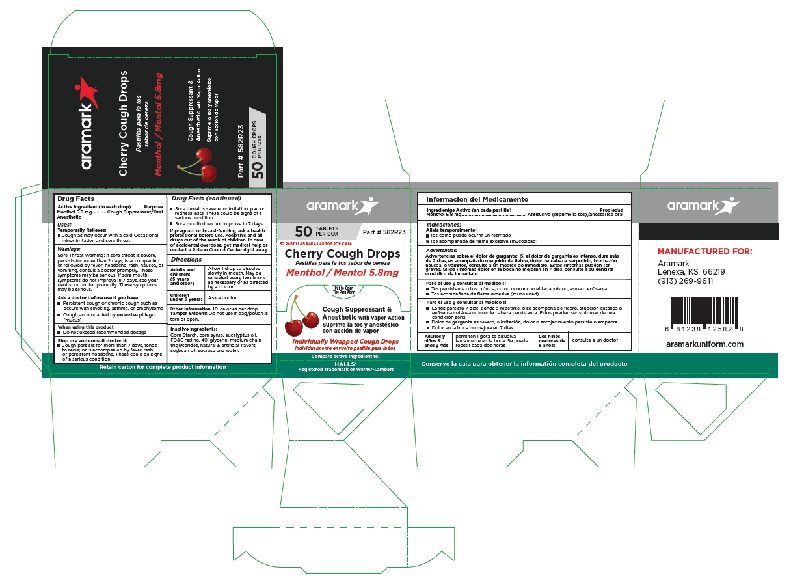 DRUG LABEL: Star Drops
NDC: 81238-5825 | Form: TABLET
Manufacturer: Western First Aid Safety DBA Aramark
Category: otc | Type: HUMAN OTC DRUG LABEL
Date: 20210618

ACTIVE INGREDIENTS: MENTHOL 5.8 mg/1 1
INACTIVE INGREDIENTS: STARCH, CORN; CORN SYRUP; EUCALYPTUS OIL; FD&C RED NO. 40; GLYCERIN; MEDIUM-CHAIN TRIGLYCERIDES; SOYBEAN OIL; SUCROSE; WATER

aramark Cherry Cough Drops

Drug Facts

Active Ingredient (in each drop)
Menthol 5.8 mg

Purpose
Cough Suppressant/Oral Anesthetic

Uses:
Temporarily Relieves:
■ Cough as may occur with a cold Occasional
minor irritation and sore throat

Warnings:

Sore Throat Warning: If sore throat is severe,
persists for more than 2 days, is accompanied
or followed by fever, headache, rash, nausea, or
vomiting, consult a doctor promptly. These
symptoms may be serious. If sore mouth
symptoms do not improve in 7 days, see your
dentist or doctor promptly. These symptoms
may be serious.

Ask a doctor before use if you have:
■ Persistent cough or chronic cough such as
occurs with smoking, asthma, or emphysema
■ Cough accompanied by excessive phlegm
(mucus)

When using this product:
■ Do not exceed recommended dosage

Stop use and consult doctor if:
■ Cough persists for more than 7 days, tends
to recur, or is accompanied by fever, rash,
or persistent headache. These could be signs
of a serious condition.
■Sore throat is severe, or irritation, pan or
redness lasts. These could be signs of a
serious condition.
■ Sore mouth does not improve in 7 days.

PREGNANCY

If pregnant or breast-feeding, ask a health
professional before use.

KEEP OUT OF REACH OF CHILDREN

Keep this and all drugs out of the reach of children. In case
of accidental overdose, get medical help or
contact a Poison Control Center right away

Directions

Adults and children: (5 years and older) | Allow 1 drop to dissolve slowly in mouth. May be repeated every two hours as necessary or as directed by a doctor.
Children under 5 years: | Ask a doctor.

Other information 10-calories per drop
Tamper Evident: Do not use if bag/pouch is
torn or open.

Inactive ingredients:
Corn Starch, corn syrup, eucalyptus oil,
FD&C red no. 40, glycerin, medium chain
triglycerides, natural & artificial flavors,
soybean oil, sucrose and water.

Package Label

aramark

Cherry Cough Drops
Menthol / Mentol 5.8mg

Cough Suppressant &
Anesthetic with Vapor Action

Individually Wrapped Cough Drops

50 TABLETS Part # 582R23
PER BOX

Compare active ingredient to:

HALLS®
Registered Trademark of Warner-Lambert

MANUFACTURED FOR:

Aramark
Lenexa, KS 66219
(913) 269-9611

Retain carton for complete product information

50 Cough Drop Package

125 Cough Drop Package

res